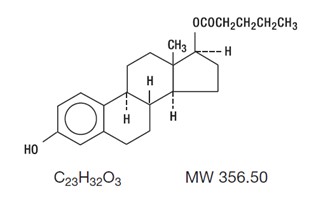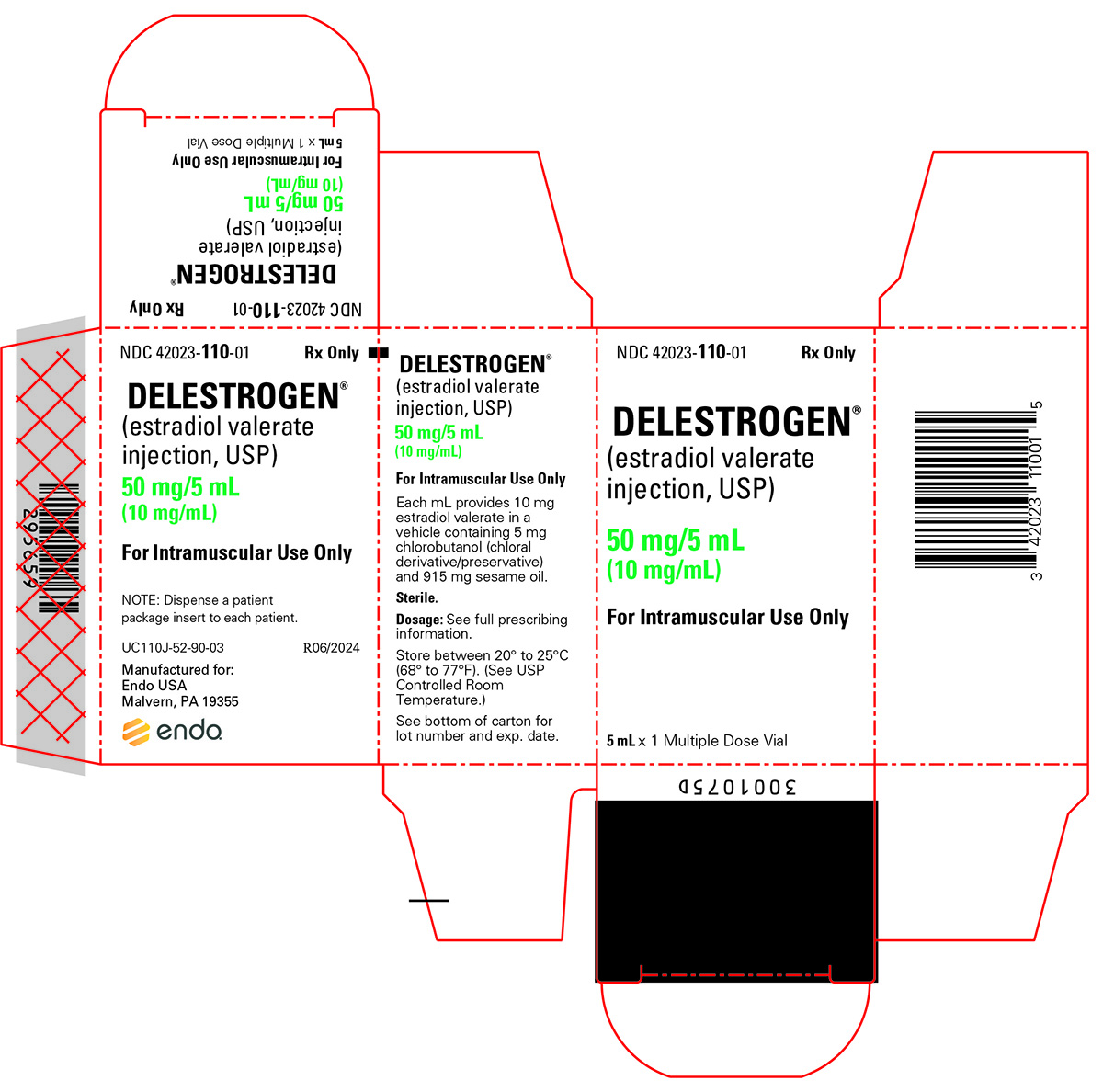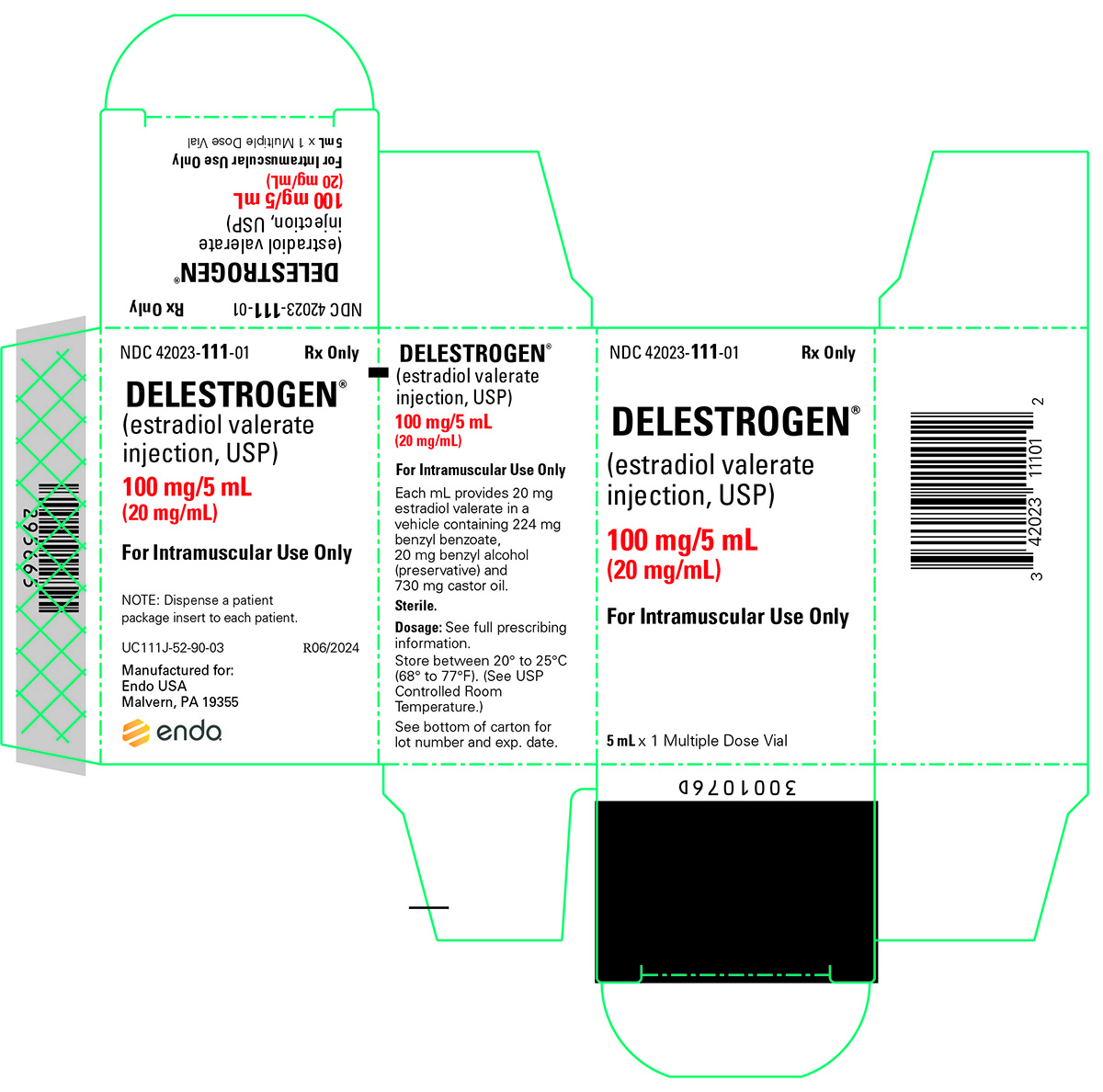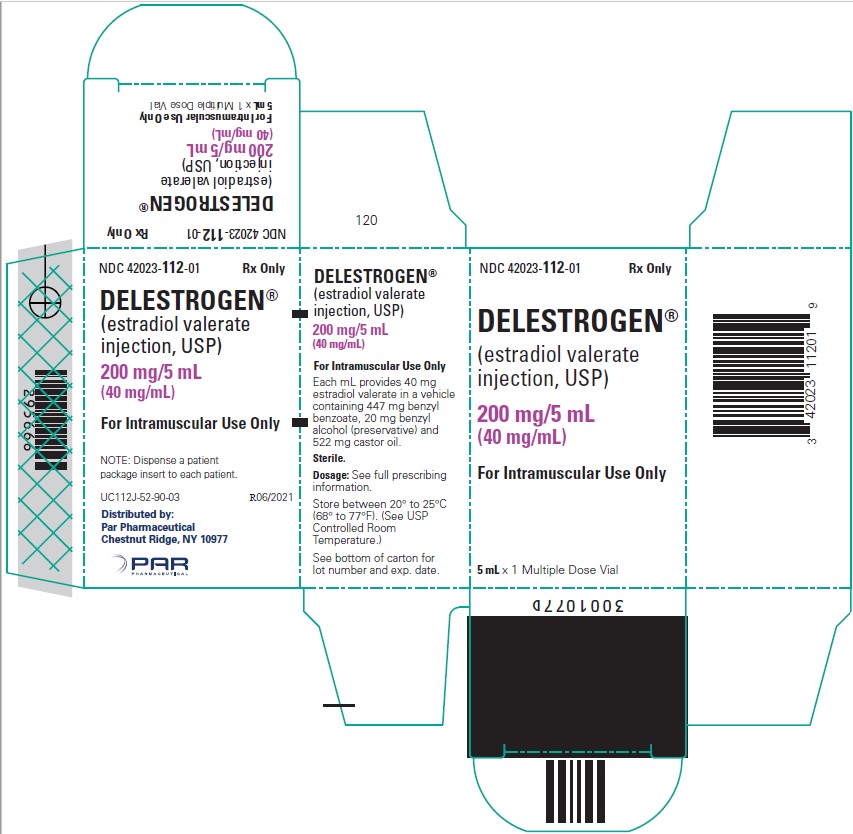 DRUG LABEL: Delestrogen
NDC: 42023-110 | Form: INJECTION
Manufacturer: Par Health USA, LLC
Category: prescription | Type: HUMAN PRESCRIPTION DRUG LABEL
Date: 20240708

ACTIVE INGREDIENTS: ESTRADIOL VALERATE 10 mg/1 mL
INACTIVE INGREDIENTS: SESAME OIL 915 mg/1 mL; CHLOROBUTANOL 5 mg/1 mL

DELESTROGEN®
(estradiol valerate injection, USP)
Rx Only

BOXED WARNING

ESTROGENS INCREASE THE RISK OF ENDOMETRIAL CANCER

Close clinical surveillance of all women taking estrogens is important. Adequate diagnostic measures, including endometrial sampling when indicated, should be undertaken to rule out malignancy in all cases of undiagnosed persistent or recurring abnormal vaginal bleeding. There is no evidence that the use of “natural” estrogens results in a different endometrial risk profile than synthetic estrogens at equivalent estrogen doses [see WARNINGS, Malignant neoplasms, Endometrial cancer].

CARDIOVASCULAR AND OTHER RISKS

Estrogens and progestins should not be used for the prevention of cardiovascular disease [see WARNINGS, Cardiovascular disorders].

The Women’s Health Initiative (WHI) study reported increased risks of myocardial infarction, stroke, invasive breast cancer, pulmonary emboli, and deep vein thrombosis in postmenopausal women (50 to 79 years of age) during 5 years of treatment with oral conjugated estrogens (CE 0.625 mg) combined with medroxyprogesterone acetate (MPA 2.5 mg) relative to placebo [see CLINICAL PHARMACOLOGY, Clinical Studies].

The Women’s Health Initiative Memory Study (WHIMS), a substudy of WHI, reported increased risk of developing probable dementia in postmenopausal women 65 years of age or older during 4 years of treatment with oral conjugated estrogens plus medroxyprogesterone acetate relative to placebo. It is unknown whether this finding applies to younger postmenopausal women or to women taking estrogen alone therapy [see CLINICAL PHARMACOLOGY, Clinical Studies].

Other doses of oral conjugated estrogens with medroxyprogesterone acetate, and other combinations and dosage forms of estrogens and progestins were not studied in the WHI clinical trials and, in the absence of comparable data, these risks should be assumed to be similar. Because of these risks, estrogens with or without progestins should be prescribed at the lowest effective doses and for the shortest duration consistent with treatment goals and risks for the individual woman.

DESCRIPTION

DELESTROGEN® (estradiol valerate injection, USP) contains estradiol valerate, a long-acting estrogen in sterile oil solutions for intramuscular use. These solutions are clear, colorless to yellow. Formulations (per mL): 10 mg estradiol valerate in a vehicle containing 5 mg chlorobutanol (chloral derivative/preservative) and 915 mg sesame oil; 20 mg estradiol valerate in a vehicle containing 224 mg benzyl benzoate, 20 mg benzyl alcohol (preservative) and 730 mg castor oil; 40 mg estradiol valerate in a vehicle containing 447 mg benzyl benzoate, 20 mg benzyl alcohol and 522 mg castor oil.

Estradiol valerate is designated chemically as estra-1,3,5(10)-triene-3, 17-diol(17β)-, 17-pentanoate. Graphic formula:

CLINICAL PHARMACOLOGY

Endogenous estrogens are largely responsible for the development and maintenance of the female reproductive system and secondary sexual characteristics. Although circulating estrogens exist in a dynamic equilibrium of metabolic interconversions, estradiol is the principal intracellular human estrogen and is substantially more potent than its metabolites, estrone and estriol, at the receptor level.

The primary source of estrogen in normally cycling adult women is the ovarian follicle, which secretes 70 to 500 mcg of estradiol daily, depending on the phase of the menstrual cycle. After menopause, most endogenous estrogen is produced by conversion of androstenedione, secreted by the adrenal cortex, to estrone by peripheral tissues. Thus, estrone and the sulfate conjugated form, estrone sulfate, are the most abundant circulating estrogens in postmenopausal women.

Estrogens act through binding to nuclear receptors in estrogen-responsive tissues. To date, two estrogen receptors have been identified. These vary in proportion from tissue to tissue.

Circulating estrogens modulate the pituitary secretion of the gonadotropins, luteinizing hormone (LH) and follicle stimulating hormone (FSH), through a negative feedback mechanism. Estrogens act to reduce the elevated levels of these hormones seen in postmenopausal women.

Pharmacokinetics

Absorption

Estrogens used in therapy are well absorbed through the skin, mucous membranes, and gastrointestinal tract. When applied for a local action, absorption is usually sufficient to cause systemic effects. When conjugated with aryl and alkyl groups for parenteral administration, the rate of absorption of oily preparations is slowed with a prolonged duration of action, such that a single intramuscular injection of estradiol valerate or estradiol cypionate is absorbed over several weeks.

Distribution

The distribution of exogenous estrogens is similar to that of endogenous estrogens. Estrogens are widely distributed in the body and are generally found in higher concentrations in the sex hormone target organs. Estrogens circulate in the blood largely bound to sex hormone binding globulin (SHBG) and albumin.

Metabolism

Exogenous estrogens are metabolized in the same manner as endogenous estrogens. Circulating estrogens exist in a dynamic equilibrium of metabolic interconversions. These transformations take place mainly in the liver. Estradiol is converted reversibly to estrone, and both can be converted to estriol, which is the major urinary metabolite. Estrogens also undergo enterohepatic recirculation via sulfate and glucuronide conjugation in the liver, biliary secretion of conjugates into the intestine, and hydrolysis in the gut followed by reabsorption. In postmenopausal women, a significant proportion of the circulating estrogens exist as sulfate conjugates, especially estrone sulfate, which serves as a circulating reservoir for the formation of more active estrogens.

When given orally, naturally-occurring estrogens and their esters are extensively metabolized (first pass effect) and circulate primarily as estrone sulfate, with smaller amounts of other conjugated and unconjugated estrogenic species. This results in limited oral potency. By contrast, synthetic estrogens, such as ethinyl estradiol and the nonsteroidal estrogens, are degraded very slowly in the liver and other tissues, which results in their high intrinsic potency. Estrogen drug products administered by non-oral routes are not subject to first-pass metabolism, but also undergo significant hepatic uptake, metabolism, and enterohepatic recycling.

Excretion

Estradiol, estrone, and estriol are excreted in the urine along with glucuronide and sulfate conjugates.

Drug Interactions

In vitro and in vivo studies have shown that estrogens are metabolized partially by cytochrome P450 3A4 (CYP3A4). Therefore, inducers or inhibitors of CYP3A4 may affect estrogen drug metabolism. Inducers of CYP3A4 such as St. John's Wort preparations (Hypericum perforatum), phenobarbital, carbamazepine, and rifampin may reduce plasma concentrations of estrogens, possibly resulting in a decrease in therapeutic effects and/or changes in the uterine bleeding profile. Inhibitors of CYP3A4 such as erythromycin, clarithromycin, ketoconazole, itraconazole, ritonavir and grapefruit juice may increase plasma concentrations of estrogens and may result in side effects.

Clinical Studies

Women's Health Initiative Studies

The Women's Health Initiative (WHI) enrolled a total of 27,000 predominantly healthy postmenopausal women to assess the risks and benefits of either the use of oral 0.625 mg conjugated estrogens (CE) per day alone or the use of oral 0.625 mg conjugated estrogens plus 2.5 mg medroxyprogesterone acetate (MPA) per day compared to placebo in the prevention of certain chronic diseases. The primary endpoint was the incidence of coronary heart disease (CHD) (nonfatal myocardial infarction and CHD death), with invasive breast cancer as the primary adverse outcome studied. A "global index" included the earliest occurrence of CHD, invasive breast cancer, stroke, pulmonary embolism (PE), endometrial cancer, colorectal cancer, hip fracture, or death due to other cause. The study did not evaluate the effects of CE or CE/MPA on menopausal symptoms.

The CE/MPA substudy was stopped early because, according to the predefined stopping rule, the increased risk of breast cancer and cardiovascular events exceeded the specified benefits included in the "global index." Results of the CE/MPA substudy, which included 16,608 women (average age of 63 years, range 50 to 79; 83.9% White, 6.5% Black, 5.5% Hispanic), after an average follow-up of 5.2 years are presented in Table 1 below:

Table 1. RELATIVE AND ABSOLUTE RISK SEEN IN THE CE/MPS SUBSTUDY OF WHIa
Eventc | Relative Risk CE/MPA vs placebo at 5.2 Years (95% CI*) | Placebo n = 8102 | CE/MPA n = 8506
Eventc | Relative Risk CE/MPA vs placebo at 5.2 Years (95% CI*) | Absolute Risk per 10,000 Person-years
CHD events | 1.29 (1.02-1.63) | 30 | 37
Non-fatal MI | 1.32 (1.02-1.72) | 23 | 30
CHD death | 1.18 (0.70-1.97) | 6 | 7
Invasive breast cancerb | 1.26 (1.00-1.59) | 30 | 38
Stroke | 1.41 (1.07-1.85) | 21 | 29
Pulmonary embolism | 2.13 (1.39-3.25) | 8 | 16
Colorectal cancer | 0.63 (0.43-0.92) | 16 | 10
Endometrial cancer | 0.83 (0.47-1.47) | 6 | 5
Hip fracture | 0.66 (0.45-0.98) | 15 | 10
Death due to cause other than the events above | 0.92 (0.74-1.14) | 40 | 37
Global Indexc | 1.15 (1.03-1.28) | 151 | 170
Deep vein thrombosisd | 2.07 (1.49-2.87) | 13 | 26
Vertebral fracturesd | 0.66 (0.44-0.98) | 15 | 9
Other osteoporotic fracturesd | 0.77 (0.69-0.86) | 170 | 131

a adapted from JAMA, 2002; 288:321-333

b includes metastatic and non-metastatic breast cancer with the exception of in situ breast cancer

c a subset of the events was combined in a “global index”, defined as the earliest occurrence of CHD events, invasive breast cancer, stroke, pulmonary embolism, endometrial cancer, colorectal cancer, hip fracture, or death due to other causes

d not included in Global Index

* nominal confidence intervals unadjusted for multiple looks and multiple comparisons

For those outcomes included in the "global index," the absolute excess risks per 10,000 women-years in the group treated with CE/MPA were 7 more CHD events, 8 more strokes, 8 more PEs, and 8 more invasive breast cancers, while absolute risk reductions per 10,000 women-years were 6 fewer colorectal cancers and 5 fewer hip fractures. The absolute excess risk of events included in the "global index" was 19 per 10,000 women-years. There was no difference between the groups in terms of all-cause mortality [see BOXED WARNING, WARNINGS, and PRECAUTIONS].

Women's Health Initiative Memory Study

The Women's Health Initiative Memory Study (WHIMS), a substudy of WHI, enrolled 4,532 predominantly healthy postmenopausal women 65 years of age and older (47% were age 65 to 69 years, 35% were 70 to 74 years, and 18% were 75 years of age and older) to evaluate the effects of CE/MPA (0.625 mg conjugated estrogens plus 2.5 mg medroxyprogesterone acetate) on the incidence of probable dementia (primary outcome) compared with placebo.

After an average follow-up of 4 years, 40 women in the estrogen/progestin group (45 per 10,000 women-years) and 21 in the placebo group (22 per 10,000 women-years) were diagnosed with probable dementia. The relative risk of probable dementia in the hormone therapy group was 2.05 (95% CI, 1.21 to 3.48) compared to placebo. Differences between groups became apparent in the first year of treatment. It is unknown whether these findings apply to younger postmenopausal women [see BOXED WARNING and WARNINGS, Dementia].

INDICATIONS AND USAGE

DELESTROGEN (estradiol valerate injection, USP) is indicated in the:

1. Treatment of moderate to severe vasomotor symptoms associated with the menopause.

2. Treatment of moderate to severe symptoms of vulvar and vaginal atrophy associated with the menopause. When prescribing solely for the treatment of symptoms of vulvar and vaginal atrophy, topical vaginal products should be considered.

3. Treatment of hypoestrogenism due to hypogonadism, castration or primary ovarian failure.

4. Treatment of advanced androgen-dependent carcinoma of the prostate (for palliation only).

CONTRAINDICATIONS

DELESTROGEN should not be used in women with any of the following conditions:

1. Undiagnosed abnormal genital bleeding.

2. Known, suspected, or history of cancer of the breast.

3. Known or suspected estrogen-dependent neoplasia.

4. Active deep vein thrombosis, pulmonary embolism or a history of these conditions.

5. Active or recent (e.g., within the past year) arterial thromboembolic disease (e.g., stroke, myocardial infarction).

6. Liver dysfunction or disease.

7. DELESTROGEN should not be used in patients with known hypersensitivity to its ingredients.

8. Known or suspected pregnancy. There is no indication for DELESTROGEN in pregnancy. There appears to be little or no increased risk of birth defects in children born to women who have used estrogens and progestins from oral contraceptives inadvertently during early pregnancy [see PRECAUTIONS].

WARNINGS

See BOXED WARNINGS.

The use of unopposed estrogens in women who have a uterus is associated with an increased risk of endometrial cancer.

1. Cardiovascular disorders

Estrogen and estrogen/progestin therapy has been associated with an increased risk of cardiovascular events such as myocardial infarction and stroke, as well as venous thrombosis and pulmonary embolism (venous thromboembolism or VTE). Should any of these occur or be suspected, estrogens should be discontinued immediately.

Risk factors for arterial vascular disease (e.g., hypertension, diabetes mellitus, tobacco use, hypercholesterolemia, and obesity) and/or venous thromboembolism (e.g., personal history or family history of VTE, obesity, and systemic lupus erythematosus) should be managed appropriately.

a. Coronary heart disease and stroke

In the Women's Health Initiative (WHI) study, an increase in the number of myocardial infarctions and strokes has been observed in women receiving CE compared to placebo. These observations are preliminary [see CLINICAL PHARMACOLOGY, Clinical Studies].

In the CE/MPA substudy of WHI, an increased risk of coronary heart disease (CHD) events (defined as non-fatal myocardial infarction and CHD death) was observed in women receiving CE/MPA compared to women receiving placebo (37 vs. 30 per 10,000 women-years). The increase in risk was observed in year one and persisted.

In the same substudy of WHI, an increased risk of stroke was observed in women receiving CE/MPA compared to women receiving placebo (29 vs. 21 per 10,000 women-years). The increase in risk was observed after the first year and persisted.

In postmenopausal women with documented heart disease (n=2,763, average age 66.7 years) a controlled clinical trial of secondary prevention of cardiovascular disease (Heart and Estrogen/Progestin Replacement Study; HERS) treatment with CE/MPA (0.625mg/2.5mg per day) demonstrated no cardiovascular benefit. During an average follow-up of 4.1 years, treatment with CE/MPA did not reduce the overall rate of CHD events in postmenopausal women with established coronary heart disease. There were more CHD events in the CE/MPA-treated group than in the placebo group in year 1, but not during the subsequent years. Two thousand three hundred and twenty one women from the original HERS trial agreed to participate in an open label extension of HERS, HERS II. Average follow-up in HERS II was an additional 2.7 years, for a total of 6.8 years overall. Rates of CHD events were comparable among women in the CE/MPA group and the placebo group in HERS, HERS II, and overall.

Large doses of estrogen (5 mg conjugated estrogens per day), comparable to those used to treat cancer of the prostate and breast, have been shown in a large prospective clinical trial in men to increase the risks of nonfatal myocardial infarction, pulmonary embolism, and thrombophlebitis.

b. Venous thromboembolism (VTE)

In the Women's Health Initiative (WHI) study, an increase in VTE has been observed in women receiving CE compared to placebo. These observations are preliminary [see CLINICAL PHARMACOLOGY, Clinical Studies].

In the CE/MPA substudy of WHI, a 2-fold greater rate of VTE, including deep venous thrombosis and pulmonary embolism, was observed in women receiving CE/MPA compared to women receiving placebo. The rate of VTE was 34 per 10,000 women-years in the CE/MPA group compared to 16 per 10,000 women-years in the placebo group. The increase in VTE risk was observed during the first year and persisted.

If feasible, estrogens should be discontinued at least 4 to 6 weeks before surgery of the type associated with an increased risk of thromboembolism, or during periods of prolonged immobilization.

2. Malignant neoplasms

a. Endometrial cancer

The use of unopposed estrogens in women with intact uteri has been associated with an increased risk of endometrial cancer. The reported endometrial cancer risk among unopposed estrogen users is about 2- to 12-fold greater than in non-users, and appears dependent on duration of treatment and on estrogen dose. Most studies show no significant increased risk associated with use of estrogens for less than one year. The greatest risk appears associated with prolonged use, with increased risks of 15- to 24-fold for five to ten years or more and this risk has been shown to persist for at least 8 to 15 years after estrogen therapy is discontinued.

Clinical surveillance of all women taking estrogen/progestin combinations is important. Adequate diagnostic measures, including endometrial sampling when indicated, should be undertaken to rule out malignancy in all cases of undiagnosed persistent or recurring abnormal vaginal bleeding. There is no evidence that the use of natural estrogens results in a different endometrial risk profile than synthetic estrogens of equivalent estrogen dose. Adding a progestin to estrogen therapy has been shown to reduce the risk of endometrial hyperplasia, which may be a precursor to endometrial cancer.

b. Breast cancer

The WHI substudy of daily CE (0.625 mg)-alone provided information about breast cancer in estrogen-alone users. In the WHI estrogen-alone substudy, after an average follow-up of 7.1 years, daily CE-alone was not associated with an increased risk of invasive breast cancer (relative risk [RR] 0.80).

After a mean follow-up of 5.6 years, the WHI substudy of daily CE (0.625 mg) plus MPA (2.5 mg) reported an increased risk of invasive breast cancer in women who took daily CE plus MPA compared to placebo. In this substudy, prior use of estrogen-alone or estrogen plus progestin therapy was reported by 26 percent of the women. The relative risk of invasive breast cancer was 1.24, and the absolute risk was 41 versus 33 cases per 10,000 women-years, for CE plus MPA compared with placebo. Among women who reported prior use of hormone therapy, the relative risk of invasive breast cancer was 1.86, and the absolute risk was 46 versus 25 cases per 10,000 women-years, for CE plus MPA compared with placebo.6 Among women who reported no prior use of hormone therapy, the relative risk of invasive breast cancer was 1.09, and the absolute risk was 40 versus 36 cases per 10,000 women-years for CE plus MPA compared with placebo. In the same substudy, invasive breast cancers were larger, were more likely to be node positive, and were diagnosed at a more advanced stage in the CE (0.625 mg) plus MPA (2.5 mg) group compared with the placebo group. Metastatic disease was rare, with no apparent difference between the two groups. Other prognostic factors, such as histologic subtype, grade and hormone receptor status did not differ between the groups [see CLINICAL STUDIES].

Consistent with the Women’s Health Initiative (WHI clinical trials), observational studies have also reported an increased risk of breast cancer for estrogen plus progestin therapy and a smaller, but still increased risk, for estrogen-alone therapy after several years of use. One large meta-analysis of prospective cohort studies reported increased risks that were dependent upon duration of use and could last up to >10 years after discontinuation of estrogen plus progestin therapy and estrogen-alone therapy. Extension of the WHI trials also demonstrated increased breast cancer risk associated with estrogen plus progestin therapy. Observational studies also suggest that the risk of breast cancer was greater, and became apparent earlier, with estrogen plus progestin therapy as compared to the risk with estrogen-alone therapy. However, these studies have not found significant variation in the risk of breast cancer among different estrogen plus progestin combinations, doses, or routes of administration.

The use of estrogen plus progestin has been reported to result in an increase in abnormal mammograms requiring further evaluation. All women should receive yearly breast examinations by a healthcare provider and perform monthly breast self-examinations. In addition, mammography examinations should be scheduled based on patient age, risk factors, and prior mammogram results.

c. Ovarian cancer

The CE/MPA substudy of WHI reported that estrogen plus progestin increased the risk of ovarian cancer. After an average follow-up of 5.6 years, the relative risk for ovarian cancer for CE/MPA versus placebo was 1.58 (95% confidence interval 0.77 – 3.24) but was not statistically significant. The absolute risk for CE/MPA versus placebo was 4.2 versus 2.7 cases per 10,000 women-years.

A meta-analysis of 17 prospective and 35 retrospective epidemiology studies found that women who used hormonal therapy for menopausal symptoms had an increased risk for ovarian cancer. The primary analysis, using case-control comparisons, included 12,110 cancer cases from the 17 prospective studies. The relative risks associated with current use of hormonal therapy was 1.41 (95% confidence interval [CI] 1.32 to 1.50); there was no difference in the risk estimates by duration of the exposure (less than 5 years [median of 3 years] vs. greater than 5 years [median of 10 years] of use before the cancer diagnosis). The relative risk associated with combined current and recent use (discontinued use within 5 years before cancer diagnosis) was 1.37 (95% CI 1.27-1.48), and the elevated risk was significant for both estrogen-alone and estrogen plus progestin products. The exact duration of hormone therapy use associated with an increased risk of ovarian cancer, however, is unknown.

3. Dementia

In the Women's Health Initiative Memory Study (WHIMS), 4,532 generally healthy postmenopausal women 65 years of age and older were studied, of whom 35% were 70 to 74 years of age and 18% were 75 or older. After an average follow-up of 4 years, 40 women being treated with CE/MPA (1.8%, n = 2,229) and 21 women in the placebo group (0.9%, n = 2,303) received diagnoses of probable dementia. The relative risk for CE/MPA versus placebo was 2.05 (95% confidence interval 1.21 – 3.48), and was similar for women with and without histories of menopausal hormone use before WHIMS. The absolute risk of probable dementia for CE/MPA versus placebo was 45 versus 22 cases per 10,000 women-years, and the absolute excess risk for CE/MPA was 23 cases per 10,000 women-years. It is unknown whether these findings apply to younger postmenopausal women [see CLINICAL PHARMACOLOGY, Clinical Studies and PRECAUTIONS, Geriatric Use].

It is unknown whether these findings apply to estrogen alone therapy.

4. Gallbladder disease

A 2- to 4-fold increase in the risk of gallbladder disease requiring surgery in postmenopausal women receiving estrogens has been reported.

5. Hypercalcemia

Estrogen administration may lead to severe hypercalcemia in patients with breast cancer and bone metastases. If hypercalcemia occurs, use of the drug should be stopped and appropriate measures taken to reduce the serum calcium level.

6. Visual abnormalities

Retinal vascular thrombosis has been reported in patients receiving estrogens. Discontinue medication pending examination if there is sudden partial or complete loss of vision, or a sudden onset of proptosis, diplopia, or migraine. If examination reveals papilledema or retinal vascular lesions, estrogens should be permanently discontinued.

PRECAUTIONS

A. GENERAL

1. Addition of a progestin when a woman has not had a hysterectomy

Studies of the addition of a progestin for 10 or more days of a cycle of estrogen administration, or daily with estrogen in a continuous regimen, have reported a lowered incidence of endometrial hyperplasia than would be induced by estrogen treatment alone. Endometrial hyperplasia may be a precursor to endometrial cancer.

There are, however, possible risks that may be associated with the use of progestins with estrogens compared to estrogen-alone regimens. These include a possible increased risk of breast cancer.

2. Elevated blood pressure

In a small number of case reports, substantial increases in blood pressure have been attributed to idiosyncratic reactions to estrogens. In a large, randomized, placebo-controlled clinical trial, a generalized effect of estrogen therapy on blood pressure was not seen. Blood pressure should be monitored at regular intervals with estrogen use.

3. Hypertriglyceridemia

In patients with pre-existing hypertriglyceridemia, estrogen therapy may be associated with elevations of plasma triglycerides leading to pancreatitis and other complications.

4. Impaired liver function and past history of cholestatic jaundice

Estrogens may be poorly metabolized in patients with impaired liver function. For patients with a history of cholestatic jaundice associated with past estrogen use or with pregnancy, caution should be exercised and in the case of recurrence, medication should be discontinued.

5. Hypothyroidism

Estrogen administration leads to increased thyroid-binding globulin (TBG) levels. Patients with normal thyroid function can compensate for the increased TBG by making more thyroid hormone, thus maintaining free T4 and T3 serum concentrations in the normal range. Patients dependent on thyroid hormone replacement therapy who are also receiving estrogens may require increased doses of their thyroid replacement therapy. These patients should have their thyroid function monitored in order to maintain their free thyroid hormone levels in an acceptable range.

6. Fluid retention

Because estrogens may cause some degree of fluid retention, patients with conditions that might be influenced by this factor, such as a cardiac or renal dysfunction, warrant careful observation when estrogens are prescribed.

7. Hypocalcemia

Estrogens should be used with caution in individuals with severe hypocalcemia.

8. Exacerbation of endometriosis

Endometriosis may be exacerbated with administration of estrogens. A few cases of malignant transformation of residual endometrial implants have been reported in women treated post-hysterectomy with estrogen alone therapy. For patients known to have residual endometriosis post-hysterectomy, the addition of progestin should be considered.

9. Exacerbation of other conditions

Estrogens may cause an exacerbation of asthma, diabetes mellitus, epilepsy, migraine or porphyria, systemic lupus erythematosus, and hepatic hemangiomas and should be used with caution in women with these conditions.

10. Hypercoagulability

Some studies have shown that women taking estrogen replacement therapy have hypercoagulability, primarily related to decreased antithrombin activity. This effect appears dose- and duration-dependent and is less pronounced than that associated with oral contraceptive use. Also, postmenopausal women tend to have increased coagulation parameters at baseline compared to premenopausal women. There is some suggestion that low dose postmenopausal mestranol may increase the risk of thromboembolism, although the majority of studies (of primarily conjugated estrogens users) report no such increase.

11. Uterine bleeding and mastodynia

Certain patients may develop undesirable manifestations of estrogenic stimulation, such as abnormal uterine bleeding and mastodynia.

B. Patient Information

Physicians are advised to discuss the PATIENT INFORMATION leaflet with patients for whom they prescribe DELESTROGEN.

C. Laboratory Tests

Estrogen administration should be initiated at the lowest dose approved for the indication and then guided by clinical response rather than by serum hormone levels (e.g., estradiol, FSH).

D. Drug/Laboratory Test Interactions

1. Accelerated prothrombin time, partial thromboplastin time, and platelet aggregation time; increased platelet count; increased factors II, VII antigen, VIII antigen, VIII coagulant activity, IX, X, XII, VII-X complex, II-VII-X complex, and beta-thromboglobulin; decreased levels of antifactor Xa and antithrombin III, decreased antithrombin III activity; increased levels of fibrinogen and fibrinogen activity; increased plasminogen antigen and activity.

2. Increased thyroid-binding globulin (TBG) levels leading to increased circulating total thyroid hormone levels as measured by protein-bound iodine (PBI), T4 levels (by column or by radioimmunoassay) or T3 levels by radioimmunoassay. T3 resin uptake is decreased, reflecting the elevated TBG. Free T4 and free T3 concentrations are unaltered. Patients on thyroid replacement therapy may require higher doses of thyroid hormone.

3. Other binding proteins may be elevated in serum (i.e., corticosteroid binding globulin (CBG), sex hormone binding globulin (SHBG)) leading to increased total circulating corticosteroids and sex steroids, respectively. Free hormone concentrations may be decreased. Other plasma proteins may be increased (angiotensinogen/renin substrate, alpha-1-antitrypsin, ceruloplasmin).

4. Increased plasma HDL and HDL2 cholesterol subfraction concentrations, reduced LDL cholesterol concentrations, increased triglycerides levels.

5. Impaired glucose tolerance.

6. Reduced response to metyrapone test.

E. Carcinogenesis, Mutagenesis, and Impairment of Fertility

Long-term continuous administration of estrogen, with and without progestin, in women with and without a uterus, has shown an increased risk of endometrial cancer, breast cancer, and ovarian cancer [see BOXED WARNINGS, WARNINGS and PRECAUTIONS].

Long-term continuous administration of natural and synthetic estrogens in certain animal species increases the frequency of carcinomas of the breast, uterus, cervix, vagina, testis, and liver.

F. Pregnancy

DELESTROGEN should not be used during pregnancy [see CONTRAINDICATIONS].

G. Nursing Mothers

Estrogen administration to nursing mothers has been shown to decrease the quantity and quality of the milk. Detectable amounts of estrogens have been identified in the milk of mothers receiving this drug. Caution should be exercised when DELESTROGEN is administered to a nursing woman.

H. Pediatric Use

Safety and effectiveness in pediatric patients have not been established. Large and repeated doses of estrogen over an extended period of time may accelerate epiphyseal closure. Therefore, periodic monitoring of bone maturation and effects on epiphyseal centers is recommended in patients in whom bone growth is not complete.

I. Geriatric Use

Clinical studies of estradiol valerate did not include sufficient numbers of subjects aged 65 and over to determine whether they respond differently from younger subjects.

In the Women's Health Initiative Memory Study, including 4,532 women 65 years of age and older, followed for an average of 4 years, 82% (n = 3,729) were 65 to 74 while 18% (n = 803) were 75 and over. Most women (80%) had no prior hormone therapy use. Women treated with conjugated estrogens plus medroxyprogesterone acetate were reported to have a two-fold increase in the risk of developing probable dementia. Alzheimer's disease was the most common classification of probable dementia in both the conjugated estrogens plus medroxyprogesterone acetate group and the placebo group. Ninety percent of the cases of probable dementia occurred in the 54% of the women that were older than 70 [see WARNINGS, Dementia].

It is unknown whether these findings apply to estrogen alone therapy.

ADVERSE REACTIONS

See BOXED WARNINGS, WARNINGS, and PRECAUTIONS.

Because clinical trials are conducted under widely varying conditions, adverse reaction rates observed in the clinical trials of a drug cannot be directly compared to rates in the clinical trials of another drug and may not reflect the rates observed in practice. The adverse reaction information from clinical trials does, however, provide a basis for identifying the adverse events that appear to be related to drug use and for approximating rates.

The following additional adverse reactions have been reported with estrogen and/or progestin therapy.

1. Genitourinary system
Changes in vaginal bleeding pattern and abnormal withdrawal bleeding or flow; breakthrough bleeding; spotting; dysmenorrhea, increase in size of uterine leiomyomata; vaginitis, including vaginal candidiasis; change in amount of cervical secretion; changes in cervical ectropion; ovarian cancer; endometrial hyperplasia; endometrial cancer.

2. Breasts

Tenderness, enlargement, pain, nipple discharge, galactorrhea; fibrocystic breast changes; breast cancer.

3. Cardiovascular

Deep and superficial venous thrombosis; pulmonary embolism; thrombophlebitis; myocardial infarction; stroke; increase in blood pressure.

4. Gastrointestinal

Nausea, vomiting; abdominal cramps, bloating; cholestatic jaundice; increased incidence of gallbladder disease; pancreatitis, enlargement of hepatic hemangiomas.

5. Skin

Chloasma or melasma, which may persist when drug is discontinued; erythema multiforme; erythema nodosum; hemorrhagic eruption; loss of scalp hair; hirsutism; pruritus, rash.

6. Eyes

Retinal vascular thrombosis; intolerance to contact lenses.

7. Central Nervous System

Headache; migraine; dizziness; mental depression; chorea; nervousness; mood disturbances; irritability; exacerbation of epilepsy, dementia.

8. Miscellaneous

Increase or decrease in weight; reduced carbohydrate tolerance; aggravation of porphyria; edema; arthalgias; leg cramps; changes in libido; urticaria, angioedema, anaphylactoid/anaphylactic reactions; hypocalcemia; exacerbation of asthma; increased triglycerides.

For medical advice about adverse reactions contact your medical professional. To report SUSPECTED ADVERSE REACTIONS, contact Endo at 1-800-828-9393 or FDA at 1-800-FDA-1088 or www.fda.gov/medwatch.

OVERDOSAGE

Serious ill effects have not been reported following acute ingestion of large doses of estrogen-containing drug products by young children. Overdosage of estrogen may cause nausea and vomiting, and withdrawal bleeding may occur in females.

DOSAGE AND ADMINISTRATION

When estrogen is prescribed for a postmenopausal woman with a uterus, progestin should also be initiated to reduce the risk of endometrial cancer. A woman without a uterus does not need progestin. Use of estrogen, alone or in combination with a progestin, should be with the lowest effective dose and for the shortest duration consistent with treatment goals and risks for the individual woman. Patients should be reevaluated periodically as clinically appropriate (e.g., 3-month to 6-month intervals) to determine if treatment is still necessary [see BOXED WARNINGS and WARNINGS]. For women who have a uterus, adequate diagnostic measures, such as endometrial sampling, when indicated, should be undertaken to rule out malignancy in cases of undiagnosed persistent or recurring abnormal vaginal bleeding.

Care should be taken to inject deeply into the upper, outer quadrant of the gluteal muscle following the usual precautions for intramuscular administration. By virtue of the low viscosity of the vehicles, the various preparations of DELESTROGEN (estradiol valerate injection, USP) may be administered with a small gauge needle (i.e., 20 Gauge x 1 1/2 inches long). Since the 40 mg potency provides a high concentration in a small volume, particular care should be observed to administer the full dose.

DELESTROGEN should be visually inspected for particulate matter and color prior to administration; the solution is clear, colorless to yellow. Storage at low temperatures may result in the separation of some crystalline material which redissolves readily on warming.

Note: A dry needle and syringe should be used. Use of a wet needle or syringe may cause the solution to become cloudy; however, this does not affect the potency of the material.

Patients should be started at the lowest dose for the indication. The lowest effective dose of DELESTROGEN has not been determined for any indication. Treated patients with an intact uterus should be monitored closely for signs of endometrial cancer, and appropriate diagnostic measures should be taken to rule out malignancy in the event of persistent or recurring abnormal vaginal bleeding. See PRECAUTIONS concerning addition of a progestin.

1. For treatment of moderate to severe vasomotor symptoms, vulvar and vaginal atrophy associated with the menopause, the lowest dose and regimen that will control symptoms should be chosen and medication should be discontinued as promptly as possible.
The usual dosage is 10 to 20 mg DELESTROGEN every four weeks.
Attempts to discontinue or taper medication should be made at 3-month to 6-month intervals.

2. For treatment of female hypoestrogenism due to hypogonadism, castration, or primary ovarian failure.
The usual dosage is 10 to 20 mg DELESTROGEN every four weeks.

3. For treatment of advanced androgen-dependent carcinoma of the prostate, for palliation only.
The usual dosage is 30 mg or more administered every one or two weeks.

HOW SUPPLIED

DELESTROGEN® (estradiol valerate injection, USP)

Multiple Dose Vials

10 mg/mL (5 mL): NDC 42023-110-01

20 mg/mL (5 mL): NDC 42023-111-01

40 mg/mL (5 mL): NDC 42023-112-01

STORAGE

Store between 20° to 25°C (68° to 77°F). (See USP Controlled Room Temperature.)

Keep out of reach of children.

PATIENT INFORMATION

DELESTROGEN®

(estradiol valerate injection, USP)

Read this PATIENT INFORMATION before you start taking DELESTROGEN and read what you get each time you refill DELESTROGEN. There may be new information. This information does not take the place of talking to your healthcare provider about your medical condition or your treatment.

BOXED WARNING

WHAT IS THE MOST IMPORTANT INFORMATION I SHOULD KNOW ABOUT DELESTROGEN (AN ESTROGEN HORMONE)?

- Estrogens increase the chances of getting cancer of the uterus.
  Report any unusual vaginal bleeding right away while you are taking estrogens. Vaginal bleeding after menopause may be a warning sign of cancer of the uterus (womb). Your healthcare provider should check any unusual vaginal bleeding to find out the cause.
- Do not use estrogens with or without progestins to prevent heart disease, heart attacks, or strokes.
  Using estrogens with or without progestins may increase your chances of getting heart attacks, strokes, breast cancer, and blood clots. Using estrogens with progestins may increase your risk of dementia. You and your healthcare provider should talk regularly about whether you still need treatment with DELESTROGEN.

What is DELESTROGEN?

DELESTROGEN is a medicine that contains estrogen hormones.

What is DELESTROGEN used for?

DELESTROGEN is used after menopause to:

- reduce moderate to severe hot flashes. Estrogens are hormones made by a woman's ovaries. The ovaries normally stop making estrogens when a woman is between 45 to 55 years old. This drop in body estrogen levels causes the "change of life" or menopause (the end of monthly menstrual periods). Sometimes, both ovaries are removed during an operation before natural menopause takes place. The sudden drop in estrogen levels causes "surgical menopause."
  When the estrogen levels begin dropping, some women develop very uncomfortable symptoms, such as feeling of warmth in the face, neck, and chest, or sudden strong feelings of heat and sweating ("hot flashes" or "hot flushes"). In some women, the symptoms are mild, and they will not need estrogens. In other women, symptoms can be more severe. You and your healthcare provider should talk regularly about whether you still need treatment with DELESTROGEN.
- treat moderate to severe dryness, itching, and burning in and around the vagina. You and your healthcare provider should talk regularly about whether you still need treatment with DELESTROGEN to control these problems. If you use DELESTROGEN only to treat your dryness, itching, and burning in and around your vagina, talk with your healthcare provider about whether a topical vaginal product would be better for you.

Who should not take DELESTROGEN?

Do not start taking DELESTROGEN if you:

- have unusual vaginal bleeding.
- currently have or have had certain cancers. Estrogens may increase the chances of getting certain types of cancers, including cancer of the breast or uterus. If you have or had cancer, talk with your healthcare provider about whether you should take DELESTROGEN.
- had a stroke or heart attack in the past year.
- currently have or have had blood clots.
- currently have or have had liver problems.
- are allergic to DELESTROGEN or any of its ingredients. See the end of this leaflet for a list of ingredients in DELESTROGEN.
- think you may be pregnant.

Tell your healthcare provider:

- if you are breastfeeding. The hormone in DELESTROGEN can pass into your milk.
- about all of your medical problems. Your healthcare provider may need to check you more carefully if you have certain conditions, such as asthma (wheezing), epilepsy (seizures), migraine, endometriosis, lupus, problems with your heart, liver, thyroid, kidneys, or have high calcium levels in your blood.
- about all the medicines you take. This includes prescription and nonprescription medicines, vitamins, and herbal supplements. Some medicines may affect how DELESTROGEN works. DELESTROGEN may also affect how your other medicines work.
- if you are going to have surgery or will be on bed rest. You may need to stop taking estrogens.

How should I take DELESTROGEN?

DELESTROGEN should be injected deeply into the upper, outer quadrant of the gluteal muscle following the usual precautions for intramuscular administration. By virtue of the low viscosity of the vehicles, the various preparations of DELESTROGEN (estradiol valerate injection, USP) may be administered with a small gauge needle (i.e., 20 Gauge x 1 1/2; inches long). Since the 40 mg potency provides a high concentration in a small volume, particular care should be observed to administer the full dose.

DELESTROGEN should be visually inspected for particulate matter and color prior to administration; the solution is clear, colorless to yellow. Storage at low temperatures may result in the separation of some crystalline material which redissolves readily on warming.

Note: A dry needle and syringe should be used. Use of a wet needle or syringe may cause the solution to become cloudy; however, this does not affect the potency of the material.

1. Start at the lowest dose and talk to your healthcare provider about how well that dose is working for you.

2. Estrogens should be used at the lowest dose possible for your treatment only as long as needed. The lowest effective dose of DELESTROGEN has not been determined. You and your healthcare provider should talk regularly (for example, every 3 to 6 months) about the dose you are taking and whether you still need treatment with DELESTROGEN.

How should I dispose of used syringes and needles?

1. Do not re-use needles or syringes.

2. Do not throw the needles and syringes in household waste. These should be discarded into an appropriate container (such as a sharps container) immediately after use. Refer to state or local laws and regulations for appropriate container requirements.

3. Make sure the container is tightly capped.

4. Strategically place the container so as to minimize handling and keep out of the reach of children.

5. Label the container indicating the presence of used needles/sharps.

6. For disposal of containers containing used needles and syringes refer to the state or local laws and regulations or as instructed by your healthcare provider or pharmacist.

7. Refer to your health care provider or pharmacist for guidance, and for additional information contact the Coalition for Safe Community Needle Disposal online at

http://www.safeneedledisposal.org or refer to the FDA website Needles and Other Sharps at http://www.fda.gov/MedicalDevices/ProductsandMedicalProcedures/HomeHealthandConsumer/ConsumerProducts/Sharps/default.htm

How should I dispose of expired or unused DELESTROGEN?

1. Do not flush unused DELESTROGEN or pour down the sink or drain.

2. Refer to the state or local laws and regulations for the safest and proper disposal of injectable medications. Contact your city or county government’s household trash and recycling service to find out if a drug take-back program is available in your community. You can also refer to your health care provider or pharmacist for guidance.

3. For additional information refer to the following FDA websites:

Disposal of Unused Medicines: What You Should Know

http://www.fda.gov/drugs/resourcesforyou/consumers/buyingusingmedicinesafely/ensuringsafeuseofmedicine/safedisposalofmedicines/ucm186187.htm

How to Dispose of Unused Medicines http://www.fda.gov/downloads/Drugs/ResourcesForYou/Consumers/BuyingUsingMedicineSafely/Understandingover-the-CounterMedicines/ucm107163.pdf

What are the possible side effects of estrogens?

Less common but serious side effects include:

- Breast cancer
- Cancer of the uterus
- Stroke
- Heart attack
- Blood clots
- Dementia
- Gallbladder disease
- Ovarian cancer

These are some of the warning signs of serious side effects:

- Breast lumps
- Unusual vaginal bleeding
- Dizziness and faintness
- Changes in speech
- Severe headaches
- Chest pain
- Shortness of breath
- Pains in your legs
- Changes in vision
- Vomiting

Call your healthcare provider right away if you get any of these warning signs, or any other unusual symptom that concerns you.

Common side effects include:

- Headache
- Breast pain
- Irregular vaginal bleeding or spotting
- Stomach/abdominal cramps, bloating
- Nausea and vomiting
- Hair loss

Other side effects include:

- High blood pressure
- Liver problems
- High blood sugar
- Fluid retention
- Enlargement of benign tumors of the uterus ("fibroids")
- Vaginal yeast infection

These are not all the possible side effects of DELESTROGEN. For more information, ask your healthcare provider or pharmacist.

What can I do to lower my chances of a serious side effect with DELESTROGEN?

Talk with your healthcare provider regularly about whether you should continue taking DELESTROGEN. If you have a uterus, talk to your healthcare provider about whether the addition of a progestin is right for you. See your healthcare provider right away if you get vaginal bleeding while taking DELESTROGEN. Have a breast exam and mammogram (breast X-ray) every year unless your healthcare provider tells you something else. If members of your family have had breast cancer or if you have ever had breast lumps or an abnormal mammogram, you may need to have breast exams more often. If you have high blood pressure, high cholesterol (fat in the blood), diabetes, are overweight, or if you use tobacco, you may have higher chances for getting heart disease. Ask your healthcare provider for ways to lower your chances for getting heart disease.

General information about safe and effective use of DELESTROGEN

Medicines are sometimes prescribed for conditions that are not mentioned in patient information leaflets. Do not take DELESTROGEN for conditions for which it was not prescribed. Do not give DELESTROGEN to other people, even if they have the same symptoms you have. It may harm them.

Keep DELESTROGEN out of the reach of children.

This leaflet provides a summary of the most important information about DELESTROGEN. If you would like more information, talk with your healthcare provider or pharmacist. You can ask for information about DELESTROGEN that is written for health professionals. You can get more information by calling the toll free number 1-800-828-9393.

What are the ingredients in DELESTROGEN?

DELESTROGEN is supplied in three 5 mL multiple dose vials; 10 mg/mL, 20 mg/mL, and 40 mg/mL strengths. The 10 mg/mL strength contains 10 mg estradiol valerate in a solution of chlorobutanol and sesame oil. The 20 mg/mL strength contains 20 mg estradiol valerate in a solution of benzyl benzoate, benzyl alcohol, and castor oil. The 40 mg/mL strength contains 40 mg estradiol valerate in a solution of benzyl benzoate, benzyl alcohol, and castor oil.

How should I store DELESTROGEN?

Store DELESTROGEN at room temperature between 20° to 25°C (68° to 77°F). (See USP Controlled Room Temperature.)

Manufactured for:

Endo USA

Malvern, PA 19355

© 2024 Endo, Inc. or one of its affiliates.

Revised: 05/2024